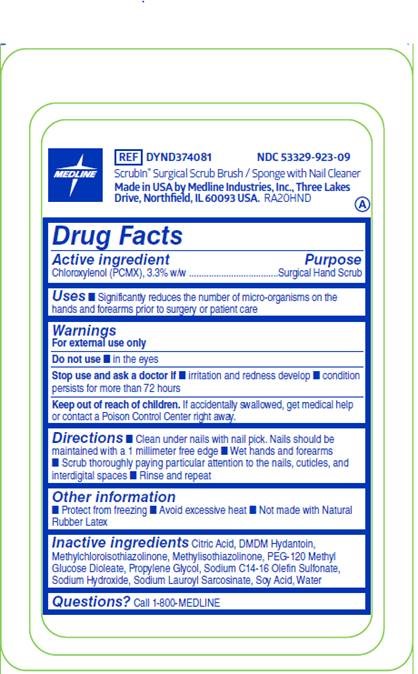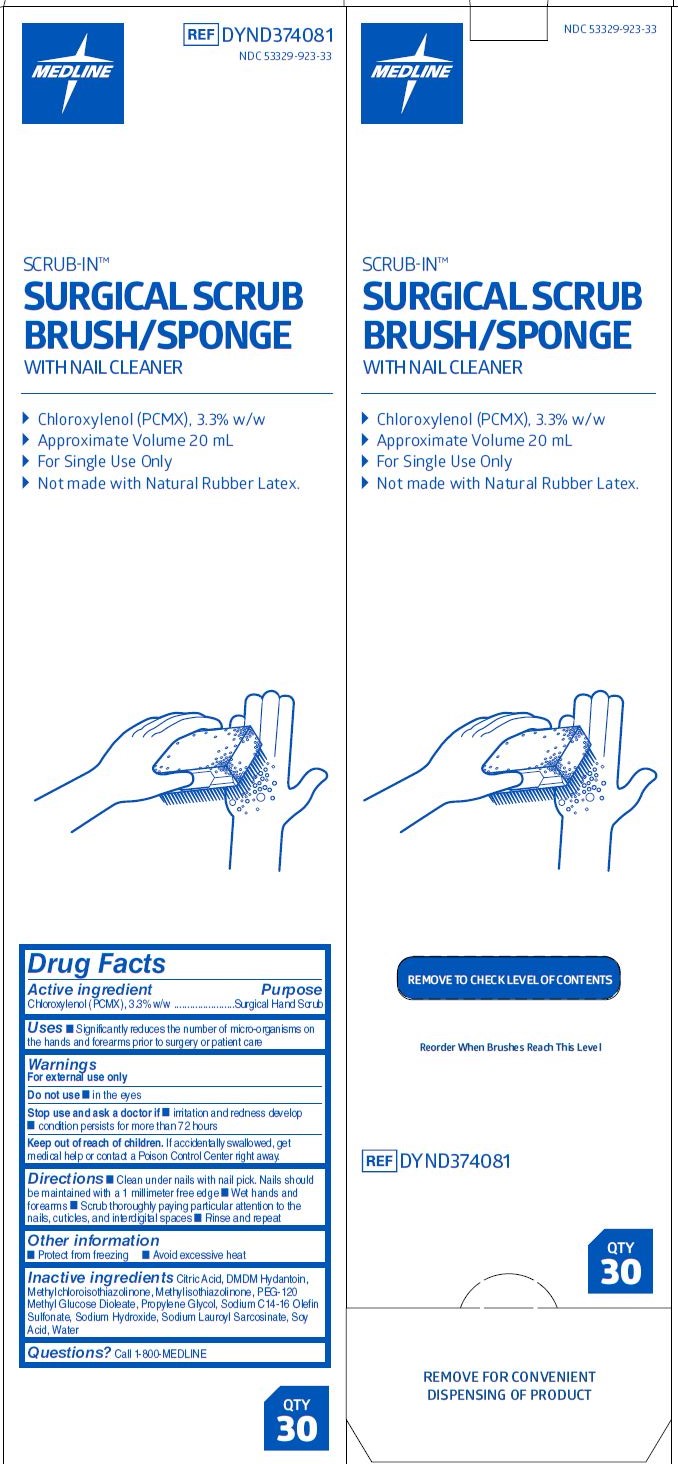 DRUG LABEL: Scrub-In Surgical Scrub Brush/Sponge
NDC: 53329-923 | Form: SOLUTION
Manufacturer: Medline Industries, LP
Category: otc | Type: HUMAN OTC DRUG LABEL
Date: 20241210

ACTIVE INGREDIENTS: CHLOROXYLENOL 3.3 mg/100 mL
INACTIVE INGREDIENTS: METHYLISOTHIAZOLINONE; CITRIC ACID MONOHYDRATE; PEG-120 METHYL GLUCOSE DIOLEATE; PROPYLENE GLYCOL; SODIUM HYDROXIDE; SODIUM LAUROYL SARCOSINATE; AMINO ACIDS, SOY; WATER; DMDM HYDANTOIN; METHYLCHLOROISOTHIAZOLINONE; SODIUM C14-16 OLEFIN SULFONATE

923 Scrubin Surgical Scrub Brush (PCMX)

Active ingredient

Chloroxylenol (PCMX), 3.3% w/w

Purpose

Surgical Hand Scrub

Uses

- Significantly reduces the number of micro-organisms on the hands and forearms prior to surgery or patient care

Warnings

For external use only

Do not use

- in the eyes

Stop use and ask a doctor if

- irritation and redness develop
- condition persists for more than 72 hours

Keep out of reach of children.

If swallowed, get medical help or contact a Poison Control Center right away.

Directions

- Clean under nails with nail pick. Nails should be maintained with a 1 millimeter free edge
- Wet hands and forearms
- Scrub thoroughly paying particular attention to the nails, cuticles, and interdigital spaces
- Rinse and repeat

Other information

- Protect from freezing
- Avoid excessive heat
- Not made with Natural Rubber Latex

Inactive ingredients

Citric Acid, DMDM Hydantoin, Methylchloroisothiazolinone, Methylisothiazolinone, PEG-120 Methyl Glucose Dioleate, Propylene Glycol, Sodium C14-16 Olefin Sulfonate, Sodium Hydroxide, Sodium Lauroyl Sarcosinate, Soy Acid, Water

Questions?

Call 1-800-MEDLINE

Manufacturing Information

Manufactured by: Medline Inustries, Inc.

THree Lakes Drive, Northfield, IL 60093 USA

Made in the USA

1-800-MEDLINE

www.medline.com

REF: DYND374081

RB20HND